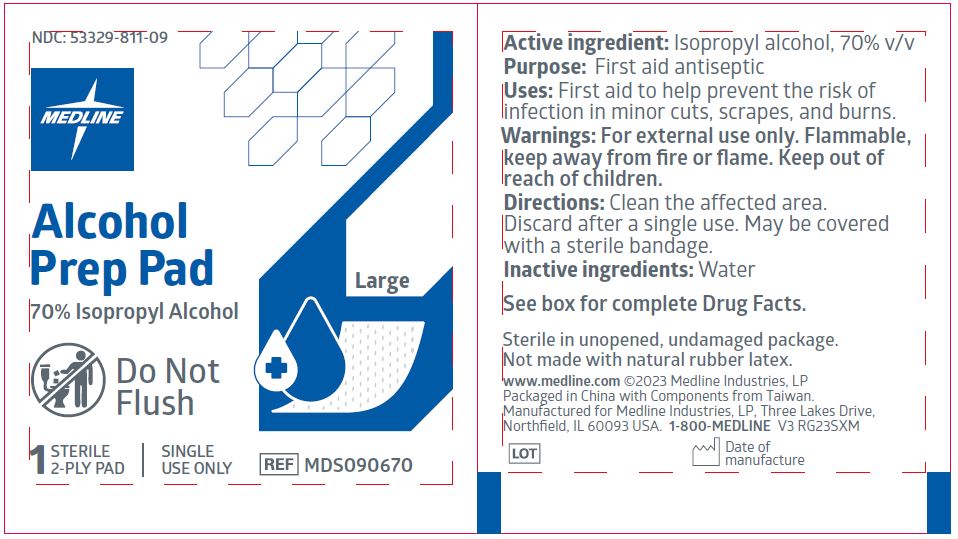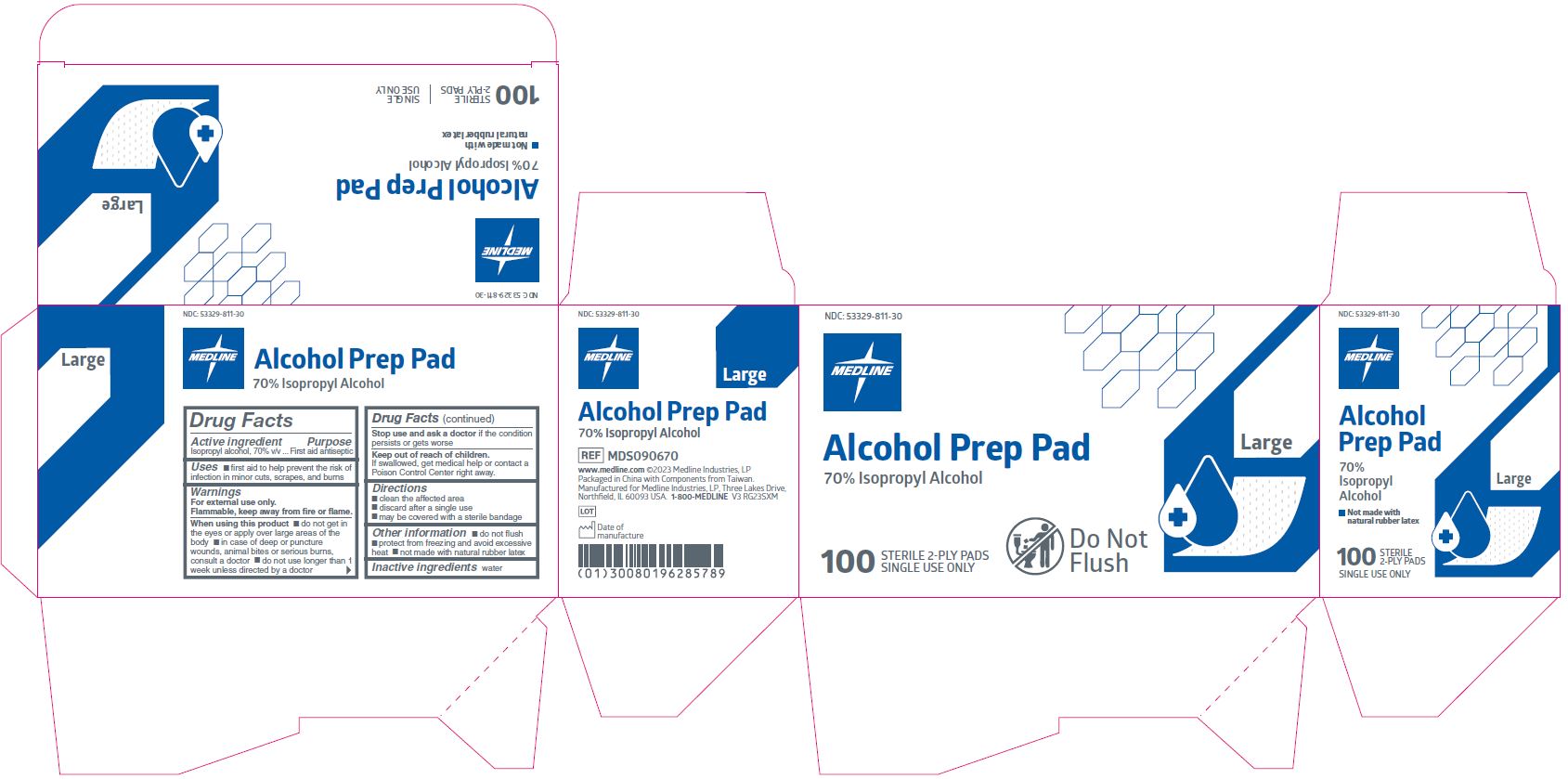 DRUG LABEL: Medline Alcohol Prep
NDC: 53329-811 | Form: SWAB
Manufacturer: Medline Industries, LP
Category: otc | Type: HUMAN OTC DRUG LABEL
Date: 20251016

ACTIVE INGREDIENTS: ISOPROPYL ALCOHOL 70 mL/100 mL
INACTIVE INGREDIENTS: WATER

811 Alcohol Prep Pad

Active ingredient

Isopropyl alcohol 70% v/v

Purpose

First aid antiseptic

Uses

- first aid to help prevent the risk of infection in minor cuts, scrapes, and burns

Warnings

For external use only.

Flammable, keep away from fire or flame.

When using this product

- do not get in the eyes or apply over large areas of the body
- in case of deep or puncture wounds, animal bites or serious burns, consult a doctor
- do not use longer than 1 week unless directed by a doctor

Stop use and ask a doctor if

- condition persists or gets worse

Keep out of reach of children.

If swallowed, get medical help or contact a Poison Control Center right away.

Directions

- clean the affected area
- discard after a single use
- may be covered with a sterile bandage

Other information

- protect from freezing, avoid excessive heat
- do not flush
- not made with natural rubber latex

Inactive ingredient

water

Manufacturing Information

www.medline.com

©2023 Medline Industries, LP

Packaged in China with Components from Taiwan.

Manufactured for Medline Industries, LP

Three Lakes Drive, Northfield, IL 60093 USA

1-800-MEDLINE (633-5463)

REF: MDS090670